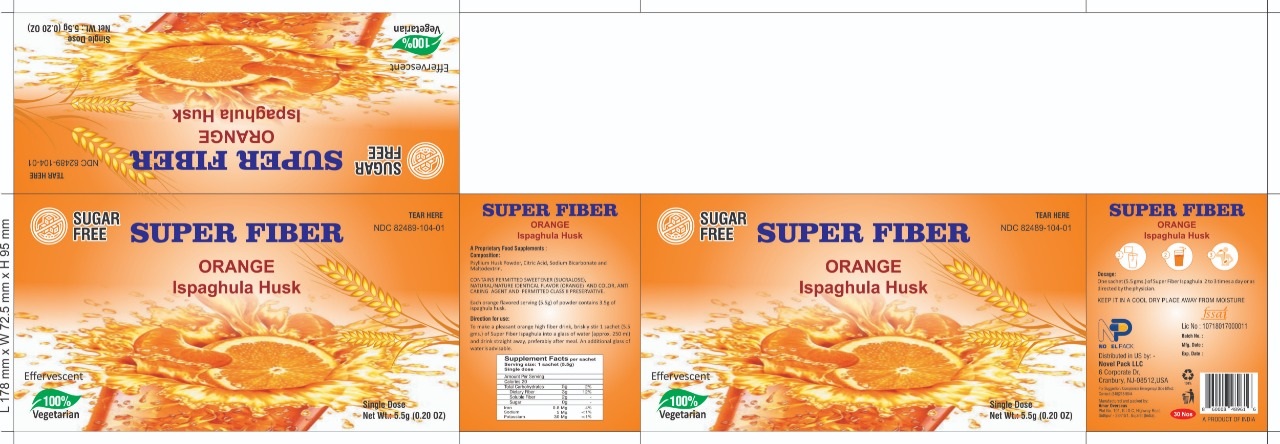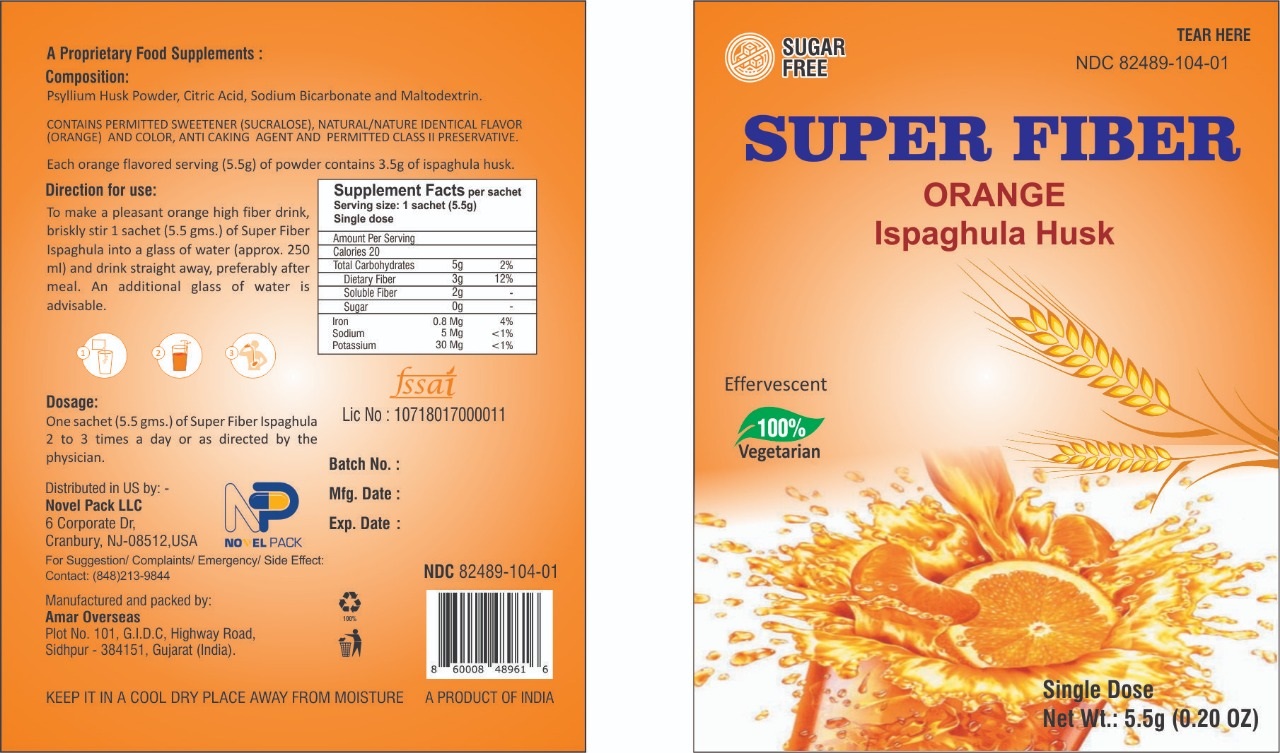 DRUG LABEL: Super Fiber
NDC: 82489-104 | Form: GRANULE, EFFERVESCENT
Manufacturer: NOVEL PACK LLC
Category: other | Type: DIETARY SUPPLEMENT
Date: 20220503

ACTIVE INGREDIENTS: PSYLLIUM HUSK 3.5 g/1 1
INACTIVE INGREDIENTS: SODIUM BICARBONATE; MALTODEXTRIN; SUCRALOSE

SUPER FIBER
ORANGE
Ispaghula Husk

STATEMENT OF IDENTITY

SUPER FIBER

Orange

Ispaghula Husk

Storage Condition

KEEP IT IN A COOL DRY PLACE AWAY FROM MOISTURE

Dosage

One sachet (5.5 gms.) of Super Fiber Ispaghula 2 to 3 times a day or as directed by the physician.

Direction for use:

To make a pleasant orange high fiber drink, briskly stir 1 sachet (5.5 gms) of Super Fiber Ispaghula into a glass of water (approx. 250 ml) and drink straight away, prefereable after meal. An additional glass of water is advisable.